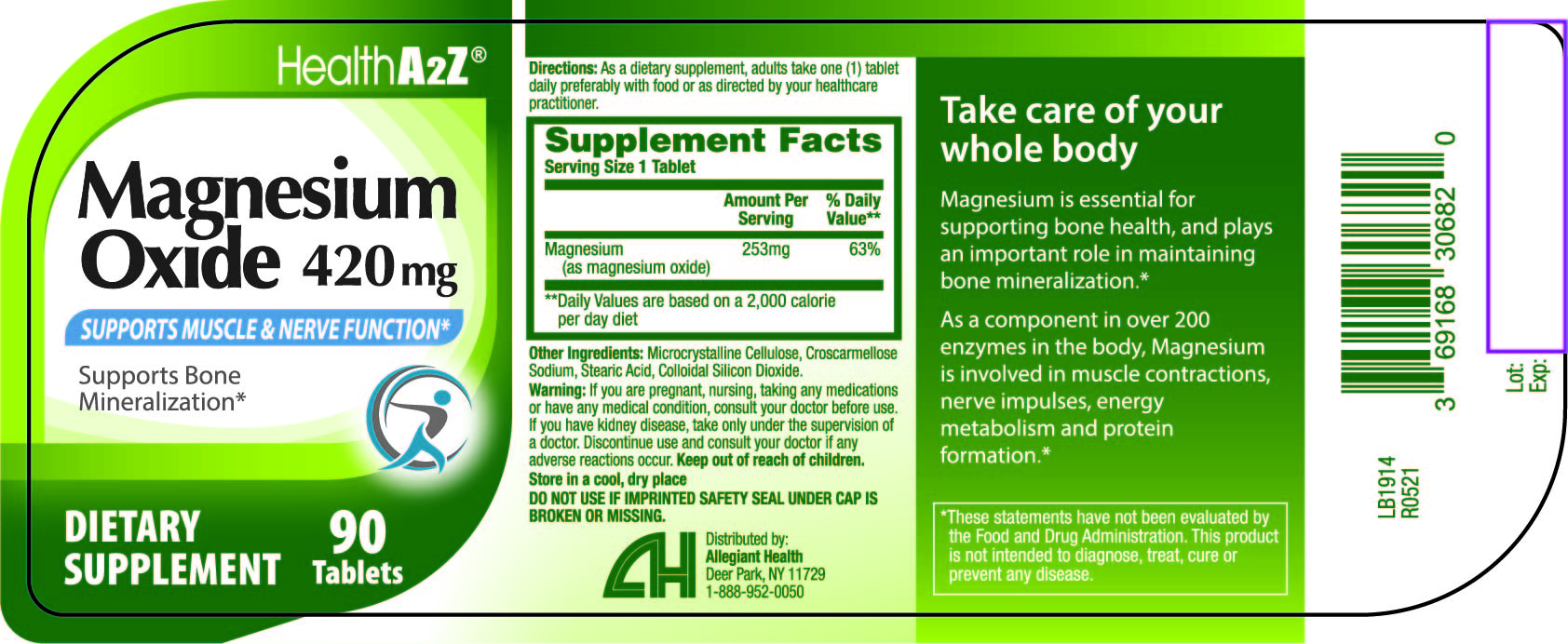 DRUG LABEL: Magnesium Oxide
NDC: 69168-306 | Form: TABLET
Manufacturer: Allegiant Health
Category: other | Type: DIETARY SUPPLEMENT
Date: 20211112

ACTIVE INGREDIENTS: MAGNESIUM OXIDE 253 mg/1 1
INACTIVE INGREDIENTS: MICROCRYSTALLINE CELLULOSE; CROSCARMELLOSE SODIUM; STEARIC ACID; SILICON DIOXIDE

Statement of Identity

STATEMENT OF IDENTITY

Magnesium (as magnesium oxide) 253mg

Ingredients

Microcrystalline Cellulose, Croscarmellose Sodium, Stearic Acid, Colloidal Silicon Dioxide.

DIRECTIONS

As a dietary supplement, adults take one (1) tablet daily preferably with food or as directed by your healthcare practitioner.

CAUTIONS

If you are pregnant, nursing, taking any medications or have any medical condition, consult your doctor before use.

If you have kidney disease, take only under the supervision of a doctor. Discontinue use and consult your doctor if any adverse reactions occur.

Keep out of reach of children.

Store in a cool, dry place

Tamper

Do not use if imprinted safety seal under cap is broken or missing.

HEALTH CLAIMS

Take care of your whole body

Magnesium is essential for supporting bone health, and plays an important role in maintaining bone mineralization*

As a component in over 200 enzymes in the body, Magnesium is involved in muscle contractions, nerve impulses, energy metabolism and protein formation*

*These statements have not been evaluated by the Food and Drug Administration. This product is not intended to diagnose, treat, cure or prevent any disease.

PRINCIPAL DISPLAY PANEL

Magnesium